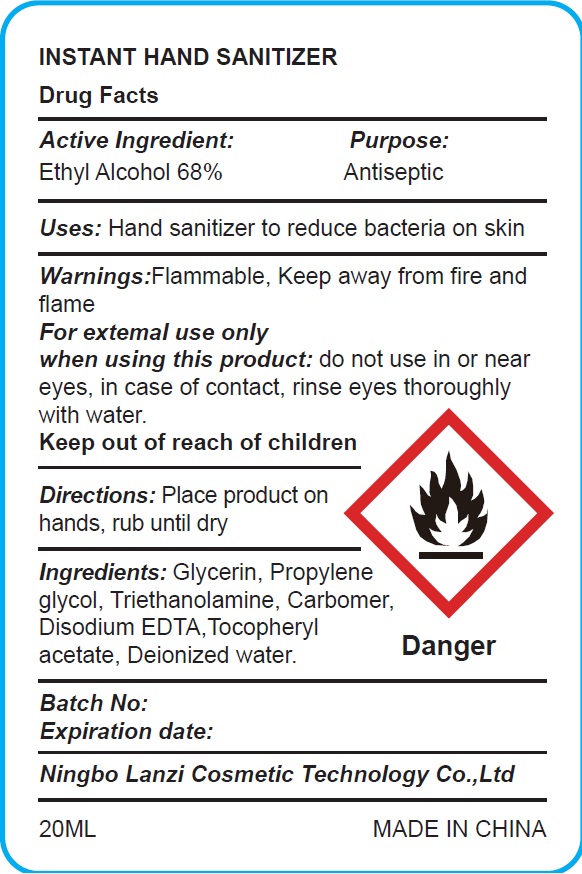 DRUG LABEL: HAND SANITIZER
NDC: 75613-018 | Form: LIQUID
Manufacturer: Ningbo Lanzi Cosmetic Technology Co., Ltd
Category: otc | Type: HUMAN OTC DRUG LABEL
Date: 20210219

ACTIVE INGREDIENTS: ALCOHOL 68 mL/100 mL
INACTIVE INGREDIENTS: WATER; PROPYLENE GLYCOL; EDETATE DISODIUM; TROLAMINE; .ALPHA.-TOCOPHEROL ACETATE, D-; GLYCERIN

HAND SANITIZER

Active ingredient

Ethyl Alcohol 68%

Purpose

Antiseptic

Use

Hand sanitizer to reduce bacteria on skin

Warnings

Flammable, keep away from fire and flame.

For external use only

When using this product

do not use in or near eyes, in case of contact, rinse eyes thoroughly with water.

Keep out of reach of children.

If swallowed, get medical help or contact a Poison Control Center right away.

Directions

Place product on hands, rub until dry.

Inactive ingredients

Glycerin, Propylene Glycol, Triethanolamine, Carbomer, Fragrance, Disodium EDTA, Tocopheryl acetate, Deionized Water